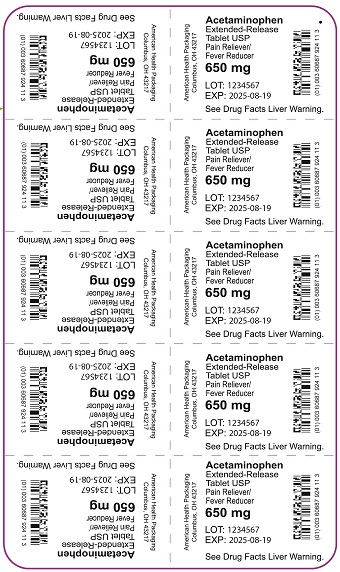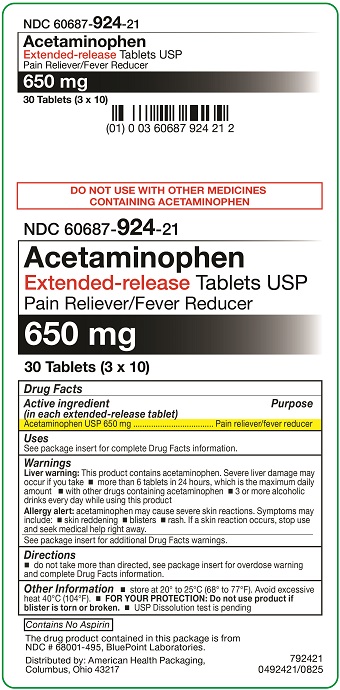 DRUG LABEL: Acetaminophen
NDC: 60687-924 | Form: TABLET
Manufacturer: American Health Packaging
Category: otc | Type: HUMAN OTC DRUG LABEL
Date: 20260204

ACTIVE INGREDIENTS: ACETAMINOPHEN 650 mg/1 1
INACTIVE INGREDIENTS: STARCH, CORN; TITANIUM DIOXIDE; TRIACETIN; SILICON DIOXIDE; POVIDONE, UNSPECIFIED; HYDROXYETHYL CELLULOSE (140 MPA.S AT 5%); MICROCRYSTALLINE CELLULOSE; SODIUM STARCH GLYCOLATE TYPE B POTATO; HYPROMELLOSE, UNSPECIFIED; MAGNESIUM STEARATE

Acetaminophen
Extended-Release
Tablets USP
Pain Reliever/Fever Reducer.
8492421/0825F

Drug Facts

Active Ingredient (in each extended release tablet)

Acetaminophen USP 650 mg

Purpose

Pain reliever/fever reducer

Uses

- temporarily relieves minor aches and pains due to:
- minor pain of arthritis
- muscular aches
- backache
- premenstrual and menstrual cramps
- the common cold
- headache
- toothache
- temporarily reduces fever

Warnings

Liver warning: This product contains acetaminophen. Severe liver damage may occur if you take

- more than 6 tablets in 24 hours, which is the maximum daily amount
- with other drugs containing acetaminophen
- 3 or more alcoholic drinks every day while using this product

Allergy alert: acetaminophen may cause severe skin reactions. Symptoms may include:

- skin reddening
- blisters
- rash

If a skin reaction occurs, stop use and seek medical help right away.

Do not use

- with any other drug containing acetaminophen (prescription or nonprescription). If you are not sure whether a drug contains acetaminophen, ask a doctor or pharmacist.
- if you are allergic to acetaminophen or any of the inactive ingredients in this product.

Ask a doctor before ue if you have liver disease.

Ask a doctor or pharmacist before use if you are taking the blood thinning drug warfarin

Stop use and ask a doctor if

- pain gets worse or lasts more than 10 days
- fever gets worse or lasts more than 3 days
- new symptoms occur
- redness or swelling is present

These could be signs of a serious condition.

If pregnant or breast-feeding, ask a health professional before use.

Keep out of reach of children.

Overdose warning: In case of overdose, get medical help or contact a Poison Control Center right away. (1-800-222-1222) Quick medical attention is critical for adults as well as for children even if you do not notice any signs or symptoms.

Directions

- do not take more than directed (see overdose warning).

Adults:

- take 2 tablets every 8 hours with water
- swallow whole; do not crush, chew, split or dissolve
- do not take more than 6 tablets in 24 hours
- do not use for more than 10 days unless directed by a doctor.

Under 18 years of age:

- ask a doctor

Other information

- store at 20º to 25ºC (68º to 77ºF). Avoid excessive heat 40ºC (104ºF)
- do not use if carton is opened or foil inner seal is broken
- USP Dissolution test is pending

Inactive ingredients

colloidal silicon dioxide, hydroxyethyl cellulose, hypromellose, magnesium stearate, microcrystalline cellulose, povidone, pregelatinized starch (maize), sodium starch glycolate, titanium dioxide, triacetin

Questions or comments?

- about the drug product, call Aurobindo Pharma USA at 1-855-274-4122
- about the packaging or labeling, call American Health Packaging at 1-800-707-4621

Contains No Aspirin

PACKAGING INFORMATION

American Health Packaging unit dose blisters contain drug product from BluePoint Laboratories as follows:
(650 mg / 30 UD) NDC 60687-924-21 packaged from NDC 68001-495

Distributed by:
American Health Packaging
Columbus, OH 43217

8492421/0825F

Principal Display Panel – Carton – 650 mg

NDC 60687- 924-21

Acetaminophen
Extended-releaseTablets USP
Pain Reliever/Fever Reducer

650 mg

30 Tablets (3 x 10)

DO NOT USE WITH OTHER MEDICINES
CONTAINING ACETAMINOPHEN.

Drug Facts

Active Ingredient Purpose
(in each caplet)
Acetaminophen USP, 650 mg.................Pain reliever/fever reducer

Uses
See package insert for complete Drug Facts information.

Warnings
Liver warning: This product contains acetaminophen. Severe liver damage may
occur if you take • more than 6 tablets in 24 hours, which is the maximum daily
amount • with other drugs containing acetaminophen • 3 or more alcoholic
drinks every day while using this product

Allergy alert: acetaminophen may cause severe skin reactions. Symptoms may
include: • skin reddening • blisters • rash If a skin reaction occurs, stop use
and seek medical help right away.

See package insert for additional Drug Facts warnings.

Directions
• do not take more than directed, see package insert for overdose warning
and complete Drug Facts information.

Other Information• store at 20° to 25°C (68° to 77°F). Avoid excessive
heat 40°C (104°F). • FOR YOURPROTECTION: Do not use product if
blister is torn or broken. •USP Dissolution test is pending

Contains No Aspirin

The drug product contained in this package is from
NDC # 68001-495, BluePoint Laboratories

Distributed by: American Health Packaging
Columbus, OH 43217

792421
0492421/0825

Principal Display Panel – Blister – 650 mg

Acetaminophen
Extended-Release
Tablet USP
Pain Reliever/
Fever Reducer

650 mg